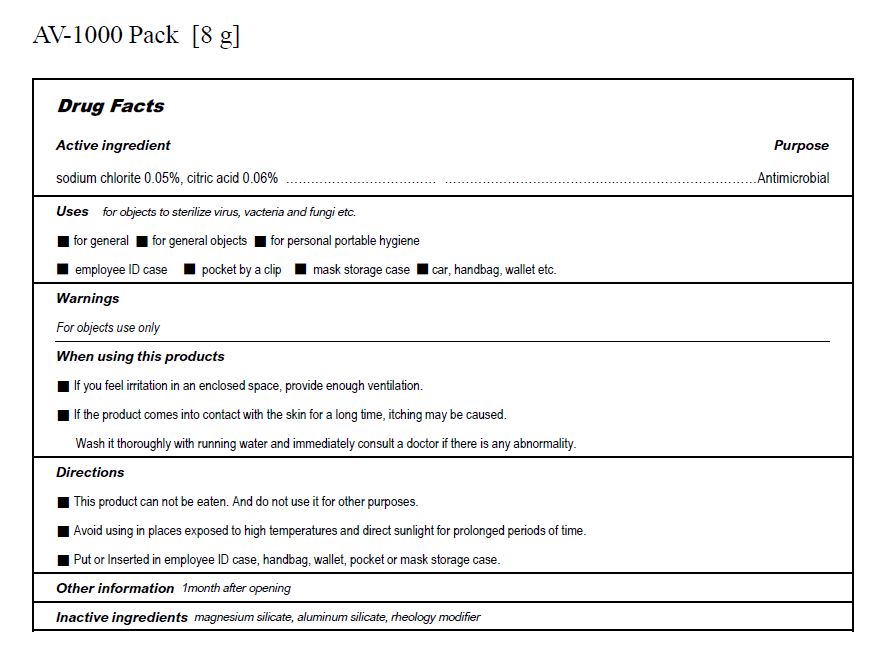 DRUG LABEL: AV-1000
NDC: 77130-0001 | Form: POWDER
Manufacturer: Sejin E&P Co., Ltd.
Category: otc | Type: HUMAN OTC DRUG LABEL
Date: 20220217

ACTIVE INGREDIENTS: CITRIC ACID MONOHYDRATE 0.06 g/100 g; SODIUM CHLORITE 0.05 g/100 g
INACTIVE INGREDIENTS: MAGNESIUM SILICATE; ALUMINUM SILICATE

Drug Facts

ACTIVE INGREDIENT

sodium chlorite 0.05%

citric acid 0.06%

INACTIVE INGREDIENT

magnesium silicate, aluminum silicate, rheology modifier

PURPOSE

for objects to sterilize virus, vacteria and fungi etc.

KEEP OUT OF REACH OF THE CHILDREN

INDICATIONS AND USAGE

This product can not be eaten. And do not use it for other purposes

Avoid using in places exposed to high temperatures and direct sunlight for prolonged periods of time.

Put or Inserted in employee ID case, handbag, wallet, pocket or mask storage case.

WARNINGS

For objects use only

If you feel irritation in an enclosed space, provide enough ventilation

If the product comes into contact with the skin for a long time, itching may be caused.
Wash it thoroughly with running water and immediately consult a doctor if there is any abnormality.

DOSAGE AND ADMINISTRATION

For objects use only